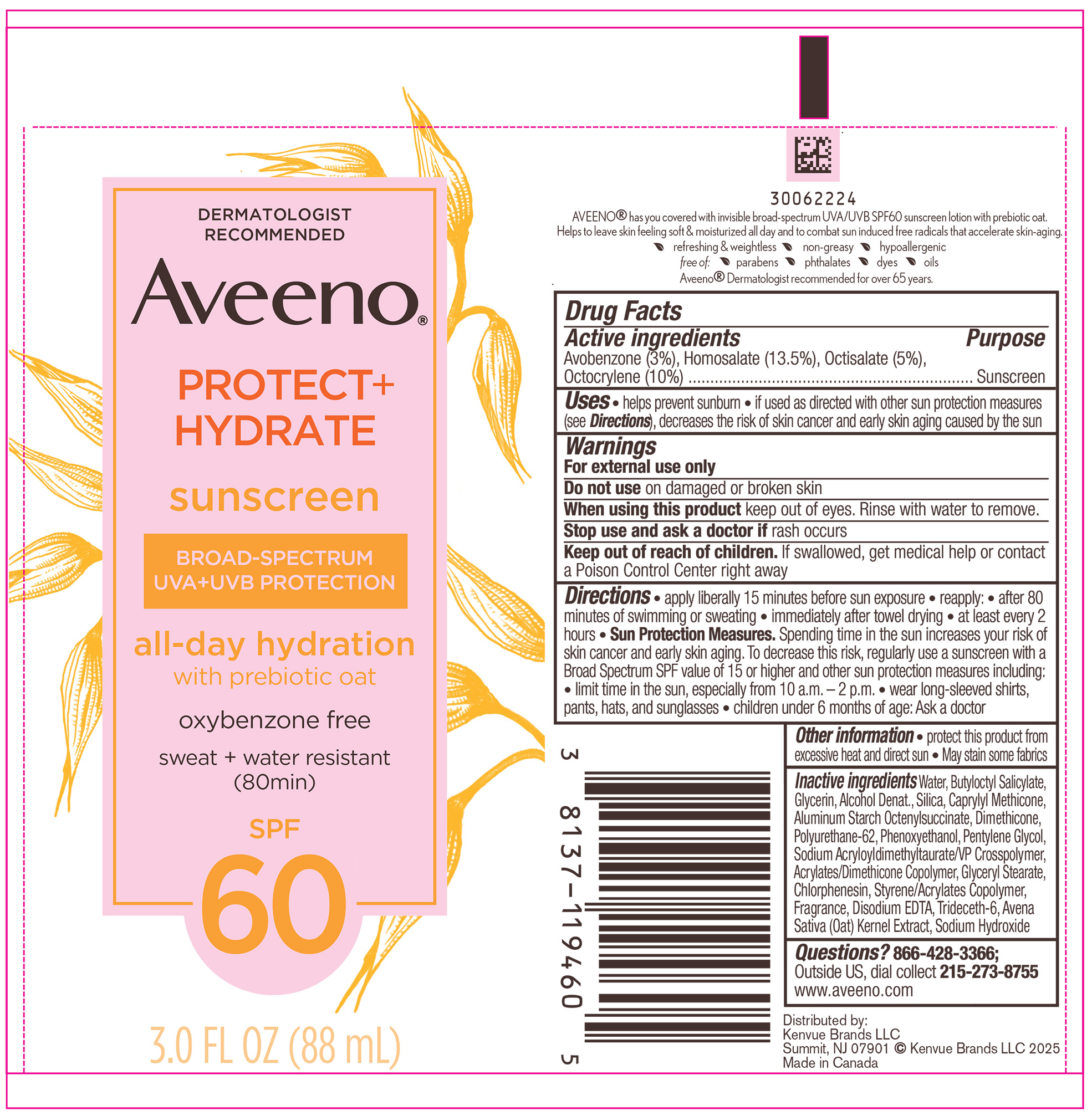 DRUG LABEL: Aveeno Protect Plus Hydrate Sunscreen Broad Spectrum Body SPF 60
NDC: 69968-0665 | Form: LOTION
Manufacturer: Kenvue Brands LLC
Category: otc | Type: HUMAN OTC DRUG LABEL
Date: 20251121

ACTIVE INGREDIENTS: AVOBENZONE 30 mg/1 mL; HOMOSALATE 135 mg/1 mL; OCTISALATE 50 mg/1 mL; OCTOCRYLENE 100 mg/1 mL
INACTIVE INGREDIENTS: POLYURETHANE-62; 2-ETHYLHEXYL ACRYLATE, METHACRYLATE, METHYL METHACRYLATE, OR BUTYL METHACRYLATE/HYDROXYPROPYL DIMETHICONE COPOLYMER (30000-300000 MW); ALCOHOL; WATER; BUTYLOCTYL SALICYLATE; GLYCERIN; SILICON DIOXIDE; CAPRYLYL TRISILOXANE; ALUMINUM STARCH OCTENYLSUCCINATE; DIMETHICONE; PHENOXYETHANOL; PENTYLENE GLYCOL; BUTYL METHACRYLATE/METHYL METHACRYLATE/METHACRYLIC ACID/STYRENE CROSSPOLYMER; GLYCERYL MONOSTEARATE; CHLORPHENESIN; EDETATE DISODIUM ANHYDROUS; TRIDECETH-6; OAT; SODIUM HYDROXIDE

Aveeno® PROTECT+ HYDRATE sunscreen BROAD-SPECTRUM Body SPF 60

Drug Facts

Active ingredients

Avobenzone 3%, Homosalate 13.5%, Octisalate 5%, Octocrylene 10%

Purpose

Sunscreen

Uses

- helps prevent sunburn
- if used as directed with other sun protection measures (see Directions), decreases the risk of skin cancer and early skin aging caused by the sun

Warnings

For external use only

- Do not use on damaged or broken skin

When using this product

- keep out of eyes. Rinse with water to remove.

Stop use and ask a doctor if rash occurs

Keep out of reach of children. If swallowed, get medical help or contact a Poison Control Center right away

Directions

- apply liberally 15 minutes before sun exposure
- reapply:
  - after 80 minutes of swimming or sweating
  - immediately after towel drying
  - at least every 2 hours
- Sun Protection Measures. Spending time in the sun increases your risk of skin cancer and early skin aging. To decrease this risk, regularly use a sunscreen with a Broad Spectrum SPF value of 15 or higher and other sun protection measures including:
  - limit time in the sun, especially from 10 a.m. – 2 p.m.
  - wear long-sleeved shirts, pants, hats, and sunglasses
- children under 6 months of age: Ask a doctor

Other information

- protect this product from excessive heat and direct sun
- may stain some fabrics

Inactive ingredients

Water, Butyloctyl Salicylate, Glycerin, Alcohol Denat., Silica, Caprylyl Methicone, Aluminum Starch Octenylsuccinate, Dimethicone, Polyurethane-62, Phenoxyethanol, Pentylene Glycol, Sodium Acryloyldimethyltaurate/VP Crosspolymer, Acrylates/Dimethicone Copolymer, Glyceryl Stearate, Chlorphenesin, Styrene/Acrylates Copolymer, Fragrance, Disodium EDTA, Trideceth-6, Avena Sativa (Oat) Kernel Extract, Sodium Hydroxide

Questions?

866-428-3366; Outside US, dial collect 215-273-8755 www.aveeno.com

Distributed by:
Kenvue Brands LLC
Summit, NJ 07901

PRINCIPAL DISPLAY PANEL - 88 mL Bottle Label

DERMATOLOGIST

RECOMMENDED

Aveeno®

PROTECT+

HYDRATE

sunscreen

BROAD-SPECTRUM

UVA + UVB PROTECTION

all-day hydration

with prebiotic oat

oxybenzone free

sweat + water resistant

(80min)

SPF

60

3.0 FL OZ (88 mL)